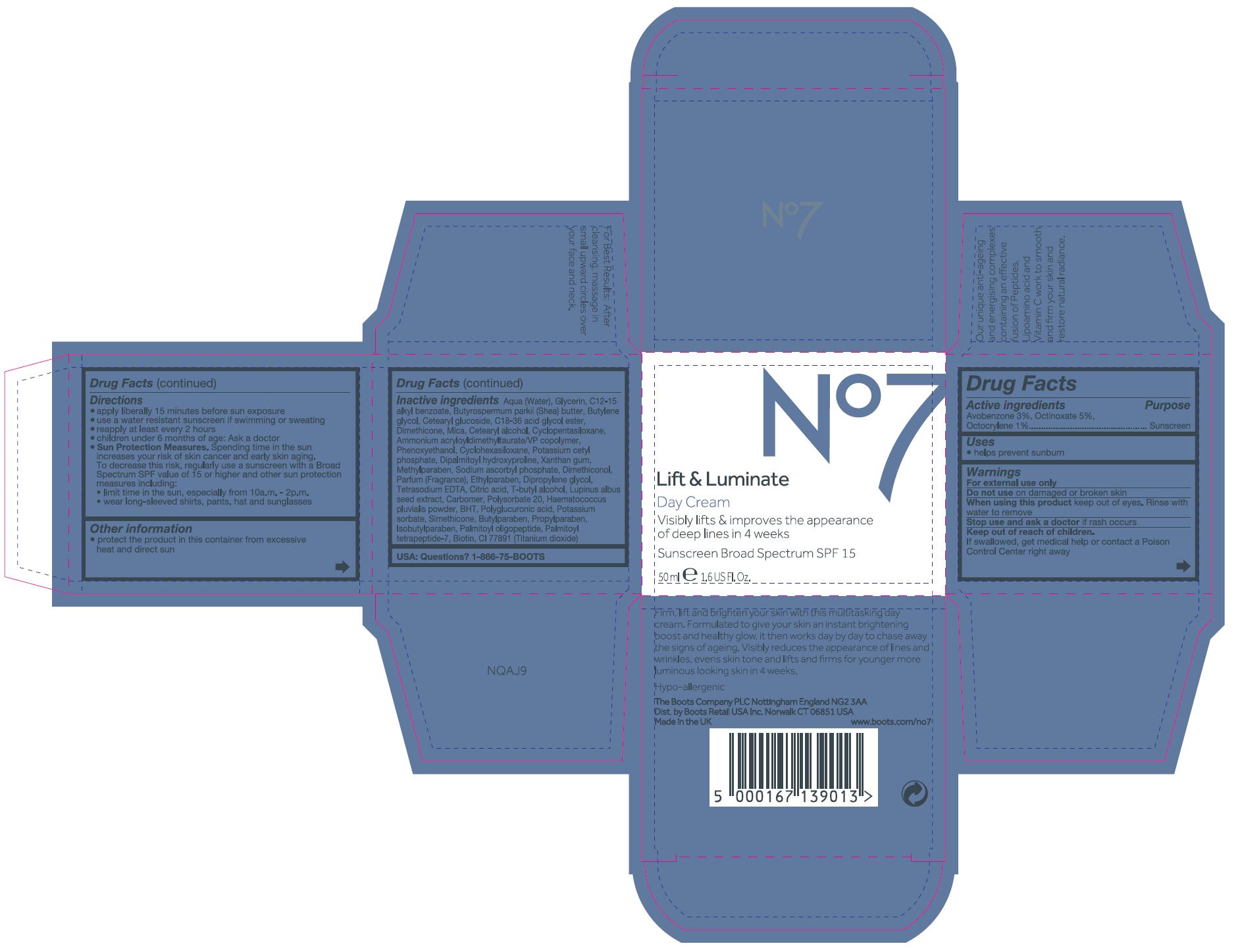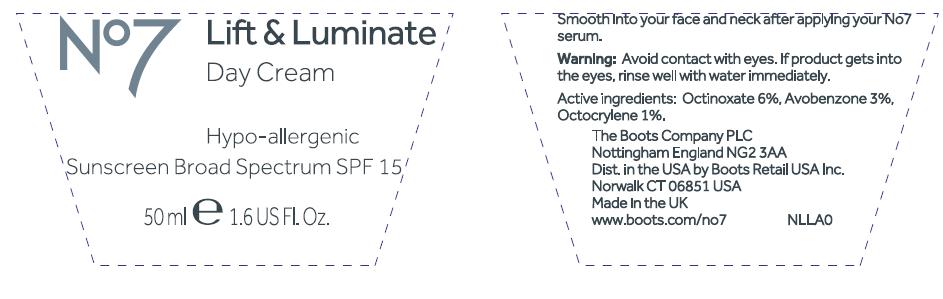 DRUG LABEL: No7 Lift and Luminate Day Sunscreen Broad Spectrum SPF 15
NDC: 68472-110 | Form: CREAM
Manufacturer: Boots Retail USA Inc
Category: otc | Type: HUMAN OTC DRUG LABEL
Date: 20120501

ACTIVE INGREDIENTS: Avobenzone 1.5 mL/50 mL; Octinoxate 2.5 mL/50 mL; Octocrylene 0.5 mL/50 mL
INACTIVE INGREDIENTS: Water; Glycerin; ALKYL (C12-15) BENZOATE; SHEA BUTTER; BUTYLENE GLYCOL; CETEARYL GLUCOSIDE; Dimethicone; mica; CETOSTEARYL ALCOHOL; CYCLOMETHICONE 5; AMMONIUM ACRYLOYLDIMETHYLTAURATE/VP COPOLYMER; Phenoxyethanol; CYCLOMETHICONE 6; POTASSIUM CETYL PHOSPHATE; DIPALMITOYL HYDROXYPROLINE; XANTHAN GUM; METHYLPARABEN; SODIUM ASCORBYL PHOSPHATE; ETHYLPARABEN; DIPROPYLENE GLYCOL; EDETATE SODIUM; CITRIC ACID MONOHYDRATE; TERT-BUTYL ALCOHOL; LUPINUS ALBUS SEED; POLYSORBATE 20; HAEMATOCOCCUS PLUVIALIS; BUTYLATED HYDROXYTOLUENE; POTASSIUM SORBATE; BUTYLPARABEN; PROPYLPARABEN; ISOBUTYLPARABEN; PALMITOYL OLIGOPEPTIDE; PALMITOYL TETRAPEPTIDE-7; biotin; TITANIUM DIOXIDE

Carton and jar labelling

Active Ingredients Avobenzone 3%, Octinoxate 5%, Octocrylene 1%

Purpose Sunscreen

PURPOSE

Uses helps prevent sunburn

Warnings

For external use only

Do not use on damaged or broken skin

When using this product keep out if eyes. Rinse with water to remove.

Stop use and ask a doctor if rash occurs.

Keep out of reach of children. If swallowed get medical help or contact a poison control center right away.

INDICATIONS AND USAGE

Directons

Apply liberally 15 minutes before sun exposure

Use a water resistant sunscreen if swimming or sweating

Reapply at least every 2 hours

Chidren under 6 months of age: Ask a doctor

Sun Protection Measures

Spending time in the sun increases your risk of skin cancer and early skin aging. To decrease this risk, regularly use a sunscreen with a broad spectrum SPF value of 15 or higher and other sun protection measures including:

limit time in the sun, especially from 10a,m - 2p.m

wear long-sleeved shirts, pants, hat and sunglasses

Other information

Protect the product in this container from excessive heat and direct sun

Inactive Ingredients

Aqua (water), Glycerin, C12-15 alkyl benzoate, Butyrospermum parkii (shea) butter, Butylene glycol, Cetearyl glucoside, C18-36 acid glycol ester, Dimethicone, Mica, Cetearyl alcohol, Cyclopentasiloxane, Ammonium acryloyldimethyltaurate/VP coplymer, Phenoxyethanol, Cyclohexasiloxane, Potassium cetyl phosphate, Dipalmitoyl hydroxyproline, Xanthan gum, Methylparaben, Sodium ascorbyl phosphate, Dimethiconol, Parfum (Fragrance), Ethylparaben, Dipropylene glycol, Tetrasodium EDTA, Citric acid, T-butyl alcohol, Lupinus albus seed extract, Carbomer, Polysorbate 20, Haematococcus Pluvialis powder, BHT, Polyglucuronic acid, Potassium sorbate, Simethicone, Butylparaben, Propylparaben, Isobutylparaben, Palmitoyl oligopeptide, Palmitoyl tetrapeptide-7, Biotin, CI 77891 (Titanium dioxide)

USA: Questions? 1-866-75-BOOTS

DESCRIPTION

Firm, lift and brighten your skin with this multitasking day cream. Formulated to give your skin an instant brightening boost and healthy glow, it then works day by day to chase away the signs of ageing. Visibly reduces the appearance of lines and wrinkles, evens skin tone and lifts and firms for younger more luminous looking skin in 4 weeks.

PATIENT COUNSELING INFORMATION

Hypoallergenic
The Boots company PLC Nottingham England NG2 3AA
Dist. by Boots Retail USA Inc. Norwalk CT 06851 USA
Made in the UK
www.Boots.com/no7

INSTRUCTIONS FOR USE

For Best Results: After cleansing, massage in small upward circles over your face and neck
Our unique anti-ageing and energising complexes containing an effective fusion of pepides, lipoamino acid and Vitamin C work to smooth and firm your skin and restore natural radiance.

ACTIVE INGREDIENT

JAR TEXT

Active ingredients: Octinoxate 6%, Avobenzone 3%, Octocrylene 1%

WARNINGS

JAR TEXT

Warning: Avoid contact with eyes. If product gets into the eyes rinse well with water immediately.

INDICATIONS AND USAGE

JAR TEXT

Smooth into your face and neck after applying your No7 serum.

PATIENT COUNSELING INFORMATION

JAR TEXT

The Boots Company PLC Nottingham England NG2 3AA
Dist. in the USA by Boots Retail USA Inc. Norwalk CT 06851 USA
Made in the UK
www.Boots.com/no7

PACKAGE LABEL

No7 Lift and Luminate

Day Cream

Visibly lifts and improves the appearance of deep lines in 4 weeks

Sunscreen broad spectrum SPF 15

50ml 1.6US Fl.Oz

No7 LL Day Cream SPF 15 carton.jpg

PACKAGE LABEL

JAR TEXT

No7 Protect and Perfect Day Cream

Hypo-allergenic

Sunscreen Broad Spectrum SPF 15

50ml 1.6 US Fl.Oz

No7 LL Day Cream SPF 15 jar.jpg